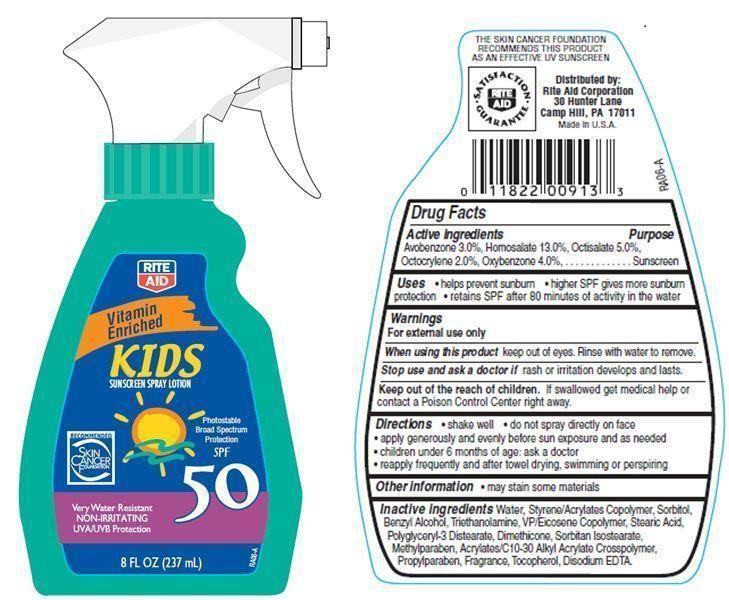 DRUG LABEL: Rite Aid Kids Sunscreen
NDC: 11822-9008 | Form: SPRAY
Manufacturer: RITE AID CORPORATION
Category: otc | Type: HUMAN OTC DRUG LABEL
Date: 20121203

ACTIVE INGREDIENTS: AVOBENZONE 3 g/100 g; HOMOSALATE 13 g/100 g; OCTISALATE 5 g/100 g; OCTOCRYLENE 2 g/100 g; OXYBENZONE 4 g/100 g
INACTIVE INGREDIENTS: WATER; DIMETHICONE; SORBITOL; TROLAMINE; STEARIC ACID; BENZYL ALCOHOL; SORBITAN ISOSTEARATE; METHYLPARABEN; PROPYLPARABEN; TOCOPHEROL; EDETATE DISODIUM

Drug Facts

Active ingredients

Avobenzone 3.0 %

Homosalate 13.0%

Octisalate 5.0%

Octocrylene 2.0%

Oxybenzone 4.0%

Purpose

Sunscreen

Uses

- helps prevent sunburn
- higher SPF gives more sunburn protection
- retains SPF after 80 minutes of activity in the water

Warnings

For external use only

When using this product

keep out of eyes. Rinse with water to remove.

Stop use and ask a doctor if

rash or irritation develops and lasts.

Keep out of reach of children

If swallowed, get medical help or contact a Poison Control Center right away.

Directions

- shake well
- do not spray directly on face
- apply generously and evenly before sun exposure and as needed
- children under 6 months of age:ask a doctor
- reapply frequently and after towel drying, swimming or perspiring.

Other Information

- may stain some materials

Inactive Ingredients

Water, Styrene/Acrylates Copolymer, Sorbitol, Benzyl Alcohol, Triethanolamine, Dimethicone, Polyglyceryl-3 Distearate, Sorbitan Isostearate, Stearic Acid, VP/Eicosene Copolymer, Acrylates/C10-30 Alkyl Acrylate Crosspolymer, Tocopherol, Disodium EDTA, Methylparaben, Propylparaben, Fragrance.

Principal Display Panel

RITE AID
Vitamin Enriched
Kids
Sunscreen
SPRAY LOTION
RECOMMENDED
SKIN CANCER FOUNDATION
Photostable
Broad Spectrum Protection
SPF 50
Very Water Resistant
NON-IRRITATING
UVA/UVB Protection
8 FL OZ (237 mL)